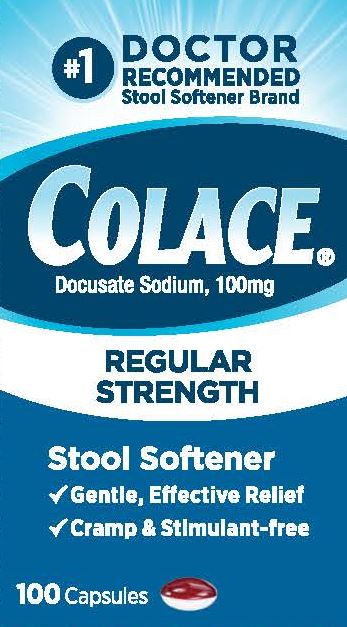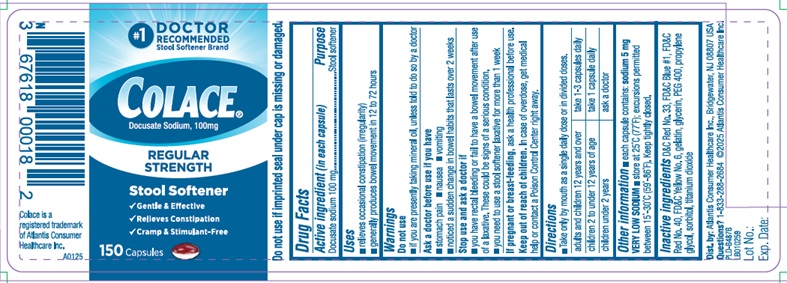 DRUG LABEL: Colace
NDC: 67618-101 | Form: CAPSULE
Manufacturer: Atlantis Consumer Healthcare, Inc.
Category: otc | Type: HUMAN OTC DRUG LABEL
Date: 20250225

ACTIVE INGREDIENTS: Docusate sodium 100 mg/1 1
INACTIVE INGREDIENTS: D&C RED NO. 33; FD&C RED NO. 40; GELATIN; GLYCERIN; POLYETHYLENE GLYCOL 400; PROPYLENE GLYCOL; SORBITOL; FD&C BLUE NO. 1; FD&C YELLOW NO. 6; TITANIUM DIOXIDE

Drug Facts

Colace 100 mg

Active ingredient (in each capsule):

Docusate sodium 100 mg

Purpose

Stool softener

Uses

- relieves occasional constipation (irregularity)
- generally produces bowel movement in 12 to 72 hours

Warnings

Do not use
- if you are presently taking mineral oil, unless told todo so by a doctor

Ask a doctor before use if you have
- stomach pain
- nausea
- vomiting
- noticed a sudden change in bowel habits that lasts over2 weeks

Stop use and ask a doctor if
- you have rectal bleeding or fail to have a bowel movementafter use of a laxative. These could be signs of a serious condition.
- you need to use a stool softener laxative for more than1 week

PREGNANCY OR BREAST FEEDING

If pregnant or breast-feeding, ask a health professional before use.

Keep out of reach of children. In caseof overdose, get medical help or contact a Poison Control Center rightaway.

Directions: Take only by mouth. Dosesmay be taken as a single daily dose or in divided doses.

adults and children 12 yearsand over | take 1-3 capsules daily
children 2 to under 12 yearsof age | take 1 capsules daily
children under 2 years | ask a doctor

STORAGE AND HANDLING

Otherinformation

- each capsule contains: sodium 5 mg VERY LOW SODIUM
- store at 25°C (77°F); excursions permitted between 15°-30°C(59°-86°F).

Keep tightly closed.

Inactive ingredients

D&C Red No. 33, FD&C Blue #1, FD&C Red No. 40,
FD&C Yellow No. 6, gelatin, glycerin, PEG
400, propylene glycol, sorbitol, titanium
dioxide

Avrio Health L.P.

304996-0A

PACKAGE LABEL

#1 DOCTOR
RECOMMENDED
Stool Softener Brand
Colace
Docusate Sodium, 100mg
REGULAR
STRENGTH
Stool Softener
√ Gentle, Effective Relief
√ Cramp & Stimulant-free
100 Capsules

#1 DOCTOR
RECOMMENDED
Stool Softener Brand
Colace®
Docusate Sodium, 100mg
REGULAR
STRENGTH
Stool Softener
√ Gentle, Effective Relief
√ Cramp & Stimulant-free
150 Capsules
Do not use if imprinted seal under cap is missing or damaged.
Colace is a
registered trademark
of Atlantis Consumer
Healthcare Inc.
A0125
Dist. by: Atlantis Consumer Healthcare Inc., Bridgewater, NJ 08807 USA
Questions? 1-833-288-2684 2025 Atlantis Consumer Healthcare Inc.
PLD-B487B
LB010259
Lot No.:
Exp. Date: